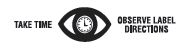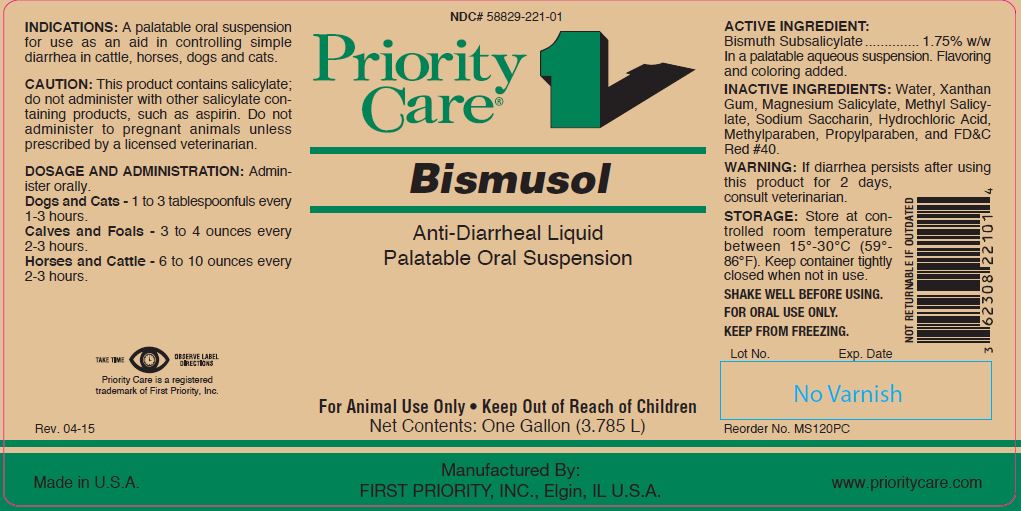 DRUG LABEL: BISMUSOL
NDC: 58829-221 | Form: SUSPENSION
Manufacturer: First Priority Incorporated
Category: animal | Type: OTC ANIMAL DRUG LABEL
Date: 20221114

ACTIVE INGREDIENTS: BISMUTH SUBSALICYLATE 17.4 g/1 L

BISMUSOL

PURPOSE

Anti-Diarrheal Liquid
Palatable Oral Suspension

KEEP OUT OF REACH OF CHILDREN

For Animal Use Only • Keep Out of Reach of Children

INDICATIONS:

A palatable oral suspension for use as an aid in controlling simple diarrhea in cattle, horses, dogs and cats.

CAUTION:

This product contains salicylate; do not administer with other salicylate-containing products, such as aspirin. Do not administer to pregnant animals unless prescribed by a licensed veterinarian.

DOSAGE AND ADMINISTRATION:

Administer orally.
Dogs and Cats - 1 to 3 tablespoonfuls every 1-3 hours.
Calves and Foals - 3 to 4 ounces every 2-3 hours.
Horses and Cattle - 6 to 10 ounces every 2-3 hours.

ACTIVE INGREDIENT:

Bismuth Subsalicylate .............. 1.75% w/w
In a palatable aqueous suspension. Flavoring and coloring added.

INACTIVE INGREDIENTS:

Water, Xanthan Gum, Magnesium Salicylate, Methyl Salicylate, Sodium Saccharin, Hydrochloric Acid, Methylparaben, Propylparaben, and FD&C Red #40.

WARNING:

If diarrhea persists after using this product for 2 days, consult veterinarian.

STORAGE:

Store at controlled room temperature between 15º to 30ºC (59º-86ºF). Keep container tightly closed when not in use.

SHAKE WELL BEFORE USING.
FOR ORAL USE ONLY.
KEEP FROM FREEZING.

Reorder No. MS120PC

Net Contents:

One Gallon (3.785 L)

INFORMATION FOR OWNERS/CAREGIVERS

Priority Care is a registered trademark of First Priority, Inc.

Made in U.S.A.

Manufactured By: FIRST PRIORITY, INC., Elgin, IL U.S.A.

www.prioritycare.com